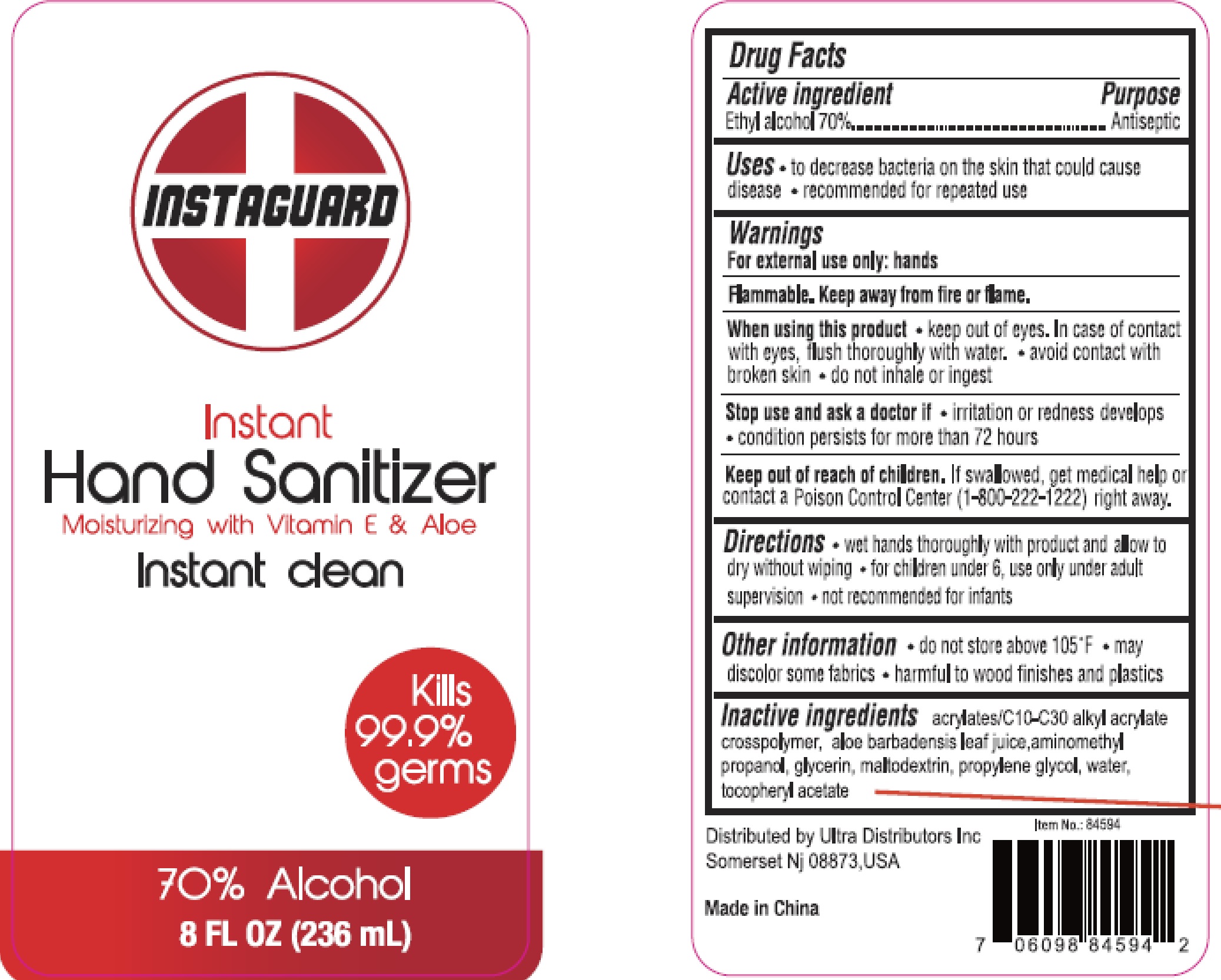 DRUG LABEL: Hand Sanitizer
NDC: 78495-008 | Form: GEL
Manufacturer: Ultra Distributors Inc.
Category: otc | Type: HUMAN OTC DRUG LABEL
Date: 20200603

ACTIVE INGREDIENTS: ALCOHOL 70 mL/100 mL
INACTIVE INGREDIENTS: MALTODEXTRIN; PROPYLENE GLYCOL; WATER; ALOE VERA LEAF; GLYCERIN; CARBOMER INTERPOLYMER TYPE A (55000 CPS); .ALPHA.-TOCOPHEROL ACETATE; AMINOMETHYLPROPANOL

Active Ingredient
Ethyl Alcohol 70%

Purpose
Antiseptic

INDICATIONS AND USAGE

Uses to decrease bacteria on the skin that could cause disease recommended for repeated use

Warnings
for external use only: hands
Flammable. Keep away from fire or flame

When using this product, keep out of eyes. In case of contact with eyes, flush thoroughly with water. avoid contact with broken skin. do not inhale or ingest.

Stop use and ask a doctor if . irritation or redness develops. condition persists for more than 72 hours

Keep out of reach of children. if swallowed, get medical help or contact a poison control center(1-800-222-1222)right away .

Directions

- wet hands thoroughly with product and allow to dry without wiping.
- for children under 6 , use only under adult supervision.
- not recommented for infants .

Other information

- do not store above 105°F
- may discolor some fabics
- harmful to wood finished and plastics

Inactive ingredients

acrylates/C10-C30 alkyl acrylate crosspolymer,aloe barbadensis leaf juice, aminomethyl propanol, glycerin, maltodextrin, propylene glycol, water , tocopheryl acetate